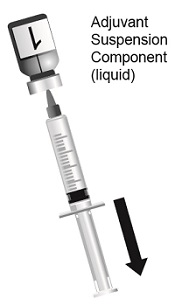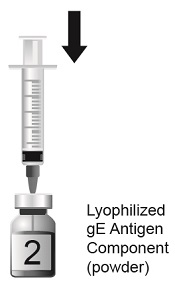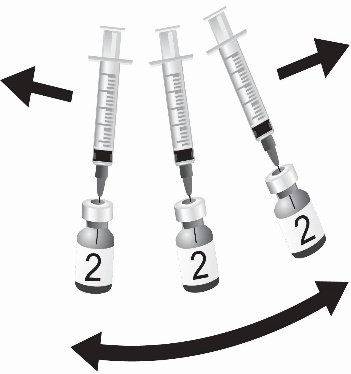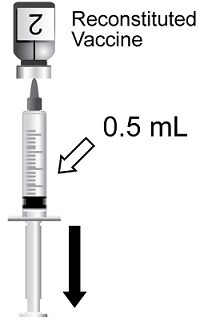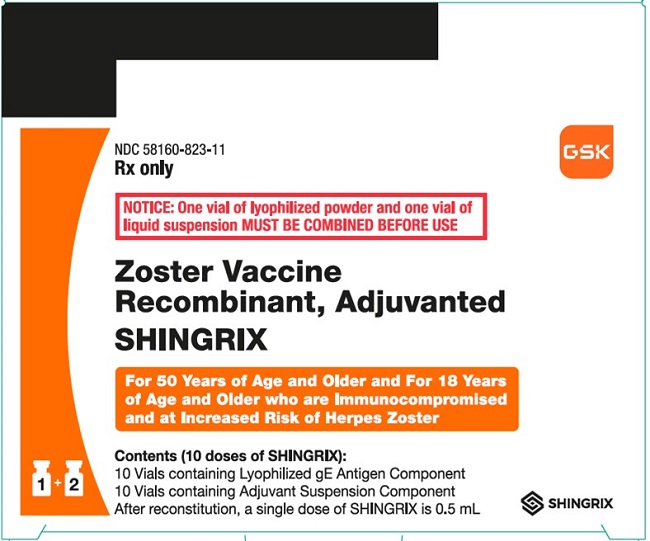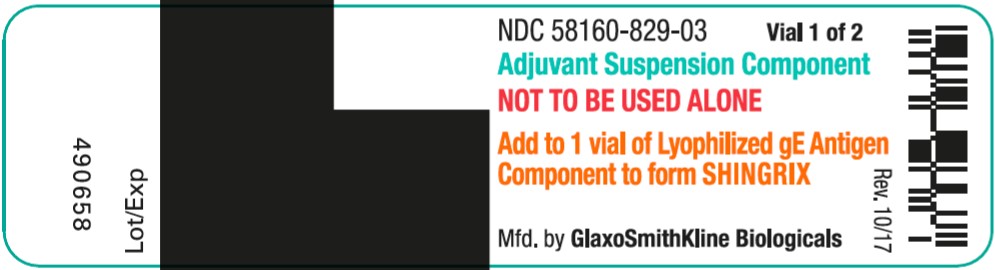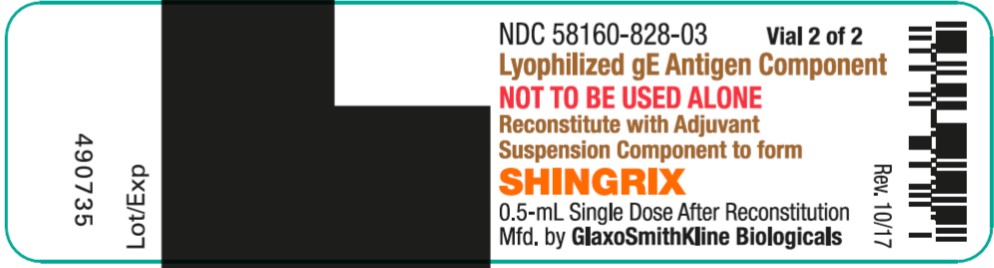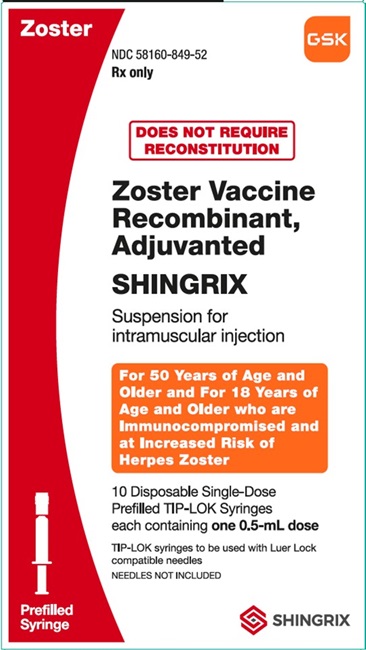 DRUG LABEL: Shingrix
NDC: 58160-823 | Form: KIT | Route: INTRAMUSCULAR
Manufacturer: GlaxoSmithKline Biologicals SA
Category: other | Type: VACCINE LABEL
Date: 20260213

ACTIVE INGREDIENTS: RECOMBINANT VARICELLA ZOSTER VIRUS GLYCOPROTEIN E ANTIGEN 50 ug/0.5 mL
INACTIVE INGREDIENTS: SUCROSE; POLYSORBATE 80; SODIUM PHOSPHATE, MONOBASIC, DIHYDRATE; DIBASIC POTASSIUM PHOSPHATE; MONOPHOSPHORYL LIPID A; QUILLAJA SAPONIN (QS-21); DIOLEOYLPHOSPHATIDYLCHOLINE, DL-; CHOLESTEROL; SODIUM PHOSPHATE, MONOBASIC, DIHYDRATE; MONOBASIC POTASSIUM PHOSPHATE; SODIUM CHLORIDE; WATER

HIGHLIGHTS OF PRESCRIBING INFORMATION

These highlights do not include all the information needed to use SHINGRIX safely and effectively. See full prescribing information for SHINGRIX.
SHINGRIX (Zoster Vaccine Recombinant, Adjuvanted) injectable suspension, for intramuscular use
Initial U.S. Approval: 2017

RECENT MAJOR CHANGES

Dosage and Administration (2.1, 2.2) | 7/2025
Warnings and Precautions, Guillain Barré Syndrome (5.2) | 2/2026

1 INDICATIONS AND USAGE

SHINGRIX is a vaccine indicated for prevention of herpes zoster (HZ) (shingles):

- in adults aged 50 years and older.
- in adults aged 18 years and older who are or will be at increased risk of HZ due to immunodeficiency or immunosuppression caused by known disease or therapy.

Limitations of Use (1):

- SHINGRIX is not indicated for prevention of primary varicella infection (chickenpox).

2 DOSAGE AND ADMINISTRATION

For intramuscular use (2).

SHINGRIX is supplied in two presentations:

Vial and Vial Presentation

The vial and vial presentation includes a vial of Lyophilized gE Antigen Component and a vial of Adjuvant Suspension Component. Reconstitute the Lyophilized gE Antigen Component with the Adjuvant Suspension Component to form SHINGRIX prior to administration. (2.1)

Prefilled Syringe Presentation

The prefilled syringe contains SHINGRIX and does not require reconstitution before use. (2.1)

Administer two doses (0.5 mL each) intramuscularly according to the following schedules:

- A first dose at Month 0 followed by a second dose administered 2 to 6 months later. (2.4)
- For individuals who are or will be immunodeficient or immunosuppressed and who would benefit from a shorter vaccination schedule: A first dose at Month 0 followed by a second dose administered 1 to 2 months later. (2.4)

3 DOSAGE FORMS AND STRENGTHS

- Injectable suspension. A single dose is 0.5 mL. (3)

4 CONTRAINDICATIONS

History of severe allergic reaction (e.g., anaphylaxis) to any component of the vaccine or after a previous dose of SHINGRIX. (4)

5 WARNINGS AND PRECAUTIONS

- In postmarketing observational studies, an increased risk of Guillain‑Barré syndrome has been observed during the 42 days following vaccination with SHINGRIX. (5.2, 6.2)
- Syncope (fainting) can be associated with the administration of injectable vaccines, including SHINGRIX. Procedures should be in place to avoid falling injury and to restore cerebral perfusion following syncope. (5.3)

6 ADVERSE REACTIONS

- Solicited local adverse reactions reported in individuals aged 50 years and older were pain (78%), redness (38%), and swelling (26%). (6.1)
- Solicited general adverse reactions reported in individuals aged 50 years and older were myalgia (45%), fatigue (45%), headache (38%), shivering (27%), fever (21%), and gastrointestinal symptoms (17%). (6.1)
- Solicited local adverse reactions reported in autologous hematopoietic stem cell transplant recipients (aged 18 through 49 and ≥50 years) were pain (88% and 83%), redness (30% and 35%), and swelling (21% and 18%). (6.1)
- Solicited general adverse reactions reported in autologous hematopoietic stem cell transplant recipients (aged 18 through 49 and ≥50 years) were fatigue (64% and 54%), myalgia (58% and 52%), headache (44% and 30%), gastrointestinal symptoms (21% and 28%), shivering (31% and 25%), and fever (28% and 18%). (6.1)

To report SUSPECTED ADVERSE REACTIONS, contact GlaxoSmithKline at 1-888-825-5249 or VAERS at 1-800-822-7967 or www.vaers.hhs.gov.

FULL PRESCRIBING INFORMATION

1 INDICATIONS AND USAGE

SHINGRIX is a vaccine indicated for prevention of herpes zoster (HZ) (shingles):

- in adults aged 50 years and older.
- in adults aged 18 years and older who are or will be at increased risk of HZ due to immunodeficiency or immunosuppression caused by known disease or therapy.

Limitations of Use:

- SHINGRIX is not indicated for prevention of primary varicella infection (chickenpox).

2 DOSAGE AND ADMINISTRATION

For intramuscular use.

2.1 SHINGRIX Presentations

SHINGRIX is supplied in two presentations, a vial and vial presentation and a prefilled syringe presentation.

Vial and Vial Presentation

The vial and vial presentation includes a vial of Lyophilized gE Antigen Component and a vial of Adjuvant Suspension Component. Reconstitute the Lyophilized gE Antigen Component with the Adjuvant Suspension Component to form SHINGRIX prior to administration.

Prefilled Syringe Presentation

The prefilled syringe contains SHINGRIX and does not require reconstitution before use.

2.2 Preparation

Reconstitution Instructions for SHINGRIX Vial and Vial Presentation

Reconstitute the Lyophilized gE Antigen Component (a sterile white powder) with the accompanying Adjuvant Suspension Component (an opalescent, colorless to pale brownish liquid) to form SHINGRIX. Use only the supplied Adjuvant Suspension Component for reconstitution. See Figures 1 through 4.

Figure 1. Cleanse both vial stoppers. Using a sterile needle appropriate for administering a vaccine intramuscularly and a sterile syringe, withdraw the entire contents of the vial containing the Adjuvant Suspension Component (liquid) by slightly tilting the vial. Vial 1 of 2.

Figure 2. Slowly transfer entire contents of syringe into the Lyophilized gE Antigen Component vial (powder). Vial 2 of 2.

Figure 3. Gently swirl the vial until powder is completely dissolved. Do not shake vigorously.

Figure 4. After reconstitution, withdraw 0.5 mL from the vial containing the reconstituted vaccine and administer intramuscularly.

After reconstitution, administer SHINGRIX immediately or store refrigerated between 2° and 8°C (36° and 46°F) and use within 6 hours. Discard reconstituted vaccine if not used within 6 hours.

Instructions for SHINGRIX Prefilled Syringe Presentation

Attach a sterile needle to the prefilled syringe and administer SHINGRIX intramuscularly.

2.3 Administration Instructions

For intramuscular use.

SHINGRIX is an opalescent, colorless to pale brownish liquid. Parenteral drug products should be inspected visually for particulate matter and discoloration prior to administration, whenever solution and container permit. If either of these conditions exists, the vaccine should not be administered.

Administer a single 0.5‑mL dose by intramuscular injection. The preferred site for intramuscular injection is the deltoid region of the upper arm.

2.4 Dose and Schedule

Administer two doses (0.5 mL each) intramuscularly according to the following schedules:

- A first dose at Month 0 followed by a second dose administered 2 to 6 months later.
- For individuals who are or will be immunodeficient or immunosuppressed and who would benefit from a shorter vaccination schedule: A first dose at Month 0 followed by a second dose administered 1 to 2 months later.

3 DOSAGE FORMS AND STRENGTHS

SHINGRIX is an injectable suspension.

A single dose is 0.5 mL.

4 CONTRAINDICATIONS

Do not administer SHINGRIX to anyone with a history of a severe allergic reaction (e.g., anaphylaxis) to any component of the vaccine or after a previous dose of SHINGRIX [see Description (11)].

5 WARNINGS AND PRECAUTIONS

5.1 Preventing and Managing Allergic Vaccine Reactions

Prior to administration, the healthcare provider should review the immunization history for possible vaccine sensitivity and previous vaccination-related adverse reactions. Appropriate medical treatment and supervision must be available to manage possible anaphylactic reactions following administration of SHINGRIX.

5.2 Guillain-Barré Syndrome (GBS)

In postmarketing observational studies, an increased risk of GBS has been observed during the 42 days following vaccination with SHINGRIX [see Adverse Reactions (6.2)].

5.3 Syncope

Syncope (fainting) can be associated with the administration of injectable vaccines, including SHINGRIX. Syncope can be accompanied by transient neurological signs such as visual disturbance, paresthesia, and tonic-clonic limb movements. Procedures should be in place to avoid falling injury and to restore cerebral perfusion following syncope.

6 ADVERSE REACTIONS

6.1 Clinical Trials Experience

Because clinical trials are conducted under widely varying conditions, adverse reaction rates observed in the clinical trials of a vaccine cannot be directly compared with rates in the clinical trials of another vaccine and may not reflect the rates observed in practice. There is the possibility that broad use of SHINGRIX could reveal adverse reactions not observed in clinical trials.

Adults Aged 50 Years and Older

Overall, 17,041 adults aged 50 years and older received at least 1 dose of SHINGRIX in 17 clinical studies.

The safety of SHINGRIX was evaluated by pooling data from 2 placebo‑controlled clinical studies (Studies 1 and 2) involving 29,305 subjects aged 50 years and older who received at least 1 dose of SHINGRIX (n = 14,645) or saline placebo (n = 14,660) administered according to a 0- and 2‑month schedule. At the time of vaccination, the mean age of the population was 69 years; 7,286 (25%) subjects were aged 50 through 59 years, 4,488 (15%) subjects were aged 60 through 69 years, and 17,531 (60%) subjects were aged 70 years and older. Both studies were conducted in North America, Latin America, Europe, Asia, and Australia. In the overall population, the majority of subjects were White (74%), followed by Asian (18%), Black (1.4%), and other racial/ethnic groups (6%); 58% were female.

Solicited Adverse Reactions: In Studies 1 and 2, data on solicited local and general adverse reactions were collected using standardized diary cards for 7 days following each vaccine dose or placebo (i.e., day of vaccination and the next 6 days) in a subset of subjects (n = 4,886 receiving SHINGRIX, n = 4,881 receiving placebo with at least 1 documented dose). Across both studies, the percentages of subjects aged 50 years and older reporting each solicited local and general adverse reaction following administration of SHINGRIX (both doses combined) were pain (78%), redness (38%), and swelling (26%); and myalgia (45%), fatigue (45%), headache (38%), shivering (27%), fever (21%), and gastrointestinal symptoms (17%).

The reported frequencies of specific solicited local adverse reactions and general adverse reactions (overall per subject), by age group, from the 2 studies are presented in Table 1.

Table 1. Percentage of Subjects with Solicited Local and General Adverse Reactions within 7 Daysa of Vaccination in Adults Aged 50 Through 59 Years, 60 Through 69 Years, and 70 Years and Olderb (Total Vaccinated Cohort with 7-Day Diary Card)
Adverse Reactions | Aged 50 Through 59 Years |  | Aged 60 Through 69 Years |  | Aged ≥70 Years
Adverse Reactions | SHINGRIX | Placeboc | SHINGRIX | Placeboc | SHINGRIX | Placeboc
Local Adverse Reactions | n = 1,315; % | n = 1,312; % | n = 1,311; % | n = 1,305; % | n = 2,258; % | n = 2,263; %
Pain | 88 | 14 | 83 | 11 | 69 | 9
Pain, Grade 3d | 10 | 1 | 7 | 1 | 4 | 0.2
Redness | 39 | 1 | 38 | 2 | 38 | 1
Redness, >100 mm | 3 | 0 | 3 | 0 | 3 | 0
Swelling | 31 | 1 | 27 | 1 | 23 | 1
Swelling, >100 mm | 1 | 0 | 1 | 0 | 1 | 0
General Adverse Reactions | n = 1,315; % | n = 1,312; % | n = 1,309; % | n = 1,305; % | n = 2,252; % | n = 2,264; %
Myalgia | 57 | 15 | 49 | 11 | 35 | 10
Myalgia, Grade 3e | 9 | 1 | 5 | 1 | 3 | 0.4
Fatigue | 57 | 20 | 46 | 17 | 37 | 14
Fatigue, Grade 3e | 9 | 2 | 5 | 1 | 4 | 1
Headache | 51 | 22 | 40 | 16 | 29 | 12
Headache, Grade 3e | 6 | 2 | 4 | 0.2 | 2 | 0.4
Shivering | 36 | 7 | 30 | 6 | 20 | 5
Shivering, Grade 3e | 7 | 0.2 | 5 | 0.3 | 2 | 0.3
Fever | 28 | 3 | 24 | 3 | 14 | 3
Fever, Grade 3f | 0.4 | 0.2 | 1 | 0.2 | 0.1 | 0.1
GIg | 24 | 11 | 17 | 9 | 14 | 8
GI, Grade 3e | 2 | 1 | 1 | 1 | 1 | 0.4
Total vaccinated cohort for safety included all subjects with at least 1 documented dose (n).
a 7 days included day of vaccination and the subsequent 6 days.
b Data for subjects aged 50 through 59 years and 60 through 69 years are based on Study 1. Data for subjects aged 70 years and older are based on pooled data from Study 1: NCT01165177 and Study 2: NCT01165229.
c Placebo was a saline solution.
d Grade 3 pain: Defined as significant pain at rest; prevents normal everyday activities.
e Grade 3 myalgia, fatigue, headache, shivering, and GI: Defined as preventing normal activity.
f Fever defined as ≥37.5°C/99.5°F for oral, axillary, or tympanic route, or ≥38°C/100.4°F for rectal route; Grade 3 fever defined as >39.0°C/102.2°F.
g GI = Gastrointestinal symptoms including nausea, vomiting, diarrhea, and/or abdominal pain.

The incidence of solicited local and general reactions was lower in subjects aged 70 years and older compared with those aged 50 through 69 years.

The local and general adverse reactions seen with SHINGRIX had a median duration of 2 to 3 days.

There were no differences in the proportions of subjects reporting any or Grade 3 solicited local reactions between Dose 1 and Dose 2. Headache and shivering were reported more frequently by subjects after Dose 2 (28% and 21%, respectively) compared with Dose 1 (24% and 14%, respectively). Grade 3 solicited general adverse reactions (headache, shivering, myalgia, and fatigue) were reported more frequently by subjects after Dose 2 (2.3%, 3%, 4%, and 4%, respectively) compared with Dose 1 (1.4%, 1.4%, 2.3%, and 2.4%, respectively).

Unsolicited Adverse Events: Unsolicited adverse events that occurred within 30 days following each vaccination (Day 0 to 29) were recorded on a diary card by all subjects. In the 2 studies, unsolicited adverse events occurring within 30 days of vaccination were reported in 51% and 32% of subjects who received SHINGRIX (n = 14,645) or placebo (n = 14,660), respectively (Total Vaccinated Cohort). Unsolicited adverse events that occurred in ≥1% of recipients of SHINGRIX and at a rate at least 1.5-fold higher than placebo included chills (4% versus 0.2%), injection site pruritus (2.2% versus 0.2%), malaise (1.7% versus 0.3%), arthralgia (1.7% versus 1.2%), nausea (1.4% versus 0.5%), and dizziness (1.2% versus 0.8%).

Gout (including gouty arthritis) was reported by 0.18% (n = 27) versus 0.05% (n = 8) of subjects who received SHINGRIX or placebo, respectively, within 30 days of vaccination; available information is insufficient to determine a causal relationship with SHINGRIX.

Serious Adverse Events (SAEs): In the 2 studies, SAEs were reported at similar rates in subjects who received SHINGRIX (2.3%) or placebo (2.2%) from the first administered dose up to 30 days post-last vaccination. SAEs were reported for 10.1% of subjects who received SHINGRIX and for 10.4% of subjects who received placebo from the first administered dose up to 1 year post-last vaccination. One subject (<0.01%) reported lymphadenitis and 1 subject (<0.01%) reported fever greater than 39°C; there was a basis for a causal relationship with SHINGRIX.

Optic ischemic neuropathy was reported in 3 subjects (0.02%) who received SHINGRIX (all within 50 days after vaccination) and 0 subjects who received placebo; available information is insufficient to determine a causal relationship with SHINGRIX.

Deaths: From the first administered dose up to 30 days post-last vaccination, deaths were reported for 0.04% of subjects who received SHINGRIX and 0.05% of subjects who received placebo in the 2 studies. From the first administered dose up to 1 year post-last vaccination, deaths were reported for 0.8% of subjects who received SHINGRIX and for 0.9% of subjects who received placebo. Causes of death among subjects were consistent with those generally reported in adult and elderly populations.

Potential Immune-Mediated Diseases: In the 2 studies, new onset potential immune-mediated diseases (pIMDs) or exacerbation of existing pIMDs were reported for 0.6% of subjects who received SHINGRIX and 0.7% of subjects who received placebo from the first administered dose up to 1 year post-last vaccination. The most frequently reported pIMDs occurred with comparable frequencies in the group receiving SHINGRIX and the placebo group.

Dosing Schedule: In an open-label clinical study, 238 subjects aged 50 years and older received SHINGRIX as a 0- and 2‑month or 0- and 6-month schedule. The safety profile of SHINGRIX was similar when administered according to a 0- and 2-month or 0- and 6-month schedule and was consistent with that observed in Studies 1 and 2.

Immunocompromised Adults Aged 18 Years and Older

The safety of SHINGRIX was evaluated in 6 placebo-controlled clinical studies that enrolled 3,116 subjects aged 18 years and older from 5 different immunodeficient or immunosuppressed (referred to as immunocompromised) populations, in which a total of 1,587 received SHINGRIX. In all studies, subjects received Doses 1 and 2 of SHINGRIX 1 to 2 months apart. Safety monitoring for these studies was similar to Studies 1 and 2. In addition, subjects were monitored for events relevant to their specific disease or condition.

At the time of receipt of SHINGRIX or placebo, the mean age of the population was 55 years; 28% subjects were aged 18 through 49 years and 72% subjects were aged 50 years and older. Each of the studies was conducted in one or more of the following regions: North America, Latin America, Europe, Asia, Africa, and Australia/New Zealand. The majority of subjects were White (77%), followed by Asian (17%), Black (2%), and other racial groups (3%); 4% were of American Hispanic or Latino ethnicity; 37% were female.

Table 2. Clinical Studies with SHINGRIX in Immunocompromised Adults Aged ≥18 Years
Clinical Studies | Number of Subjects Vaccinated |  | Study Population | Safety Follow‑up Period
Clinical Studies | SHINGRIX | Placebo | Study Population | Safety Follow‑up Period
auHSCT (NCT01610414) | 922 | 924 | Autologous hematopoietic stem cell transplant recipientsa | 29 months median safety follow-upb
Hematologic Malignancies (NCT01767467) | 283 | 279 | Hematologic malignanciesc,d | 12 months post-last vaccination
Renal Transplant; (NCT02058589) | 132 | 132 | Renal transplant recipientse | 12 months post-last vaccination
Solid Malignant Tumors (NCT01798056) | 117 | 115 | Solid tumors receiving chemotherapyf,g | 12 months post-last vaccination
HIV (NCT01165203) | 74 | 49 | HIV-infected subjects | 12 months post-last vaccination
auHSCT (NCT00920218) | 59 | 30 | Autologous hematopoietic stem cell transplant recipientsa | 12 months post-last vaccination
a The first dose was administered within 50 to 70 days after autologous hematopoietic stem cell transplantation.
b Safety follow-up was driven by HZ case accrual and ranged from a minimum of 12 months post-last vaccination to 4 years at subject level.
c For subjects who were vaccinated during a cancer therapy course, each dose was administered with at least 10 days between vaccination and cancer therapy cycles.
d For subjects who received the vaccination after a full cancer therapy course, the first dose was administered from 10 days to 6 months after cancer therapy had ended.
e The first dose was administered between 4 to 18 months after renal transplantation.
f In the PreChemo group (TVC: SHINGRIX [n = 90], placebo [n = 91]), the first dose was administered a maximum of 1 month to a minimum of 10 days before the start of a chemotherapy cycle, and the second dose was administered on the first day of a chemotherapy cycle.
g In the OnChemo group (TVC: SHINGRIX [n = 27], placebo [n = 24]), each dose was administered on the first day of a chemotherapy cycle.

In the auHSCT study (NCT01610414), at the time of receipt of SHINGRIX or placebo, the mean age of the population was 55 years; 25% of subjects were aged 18 through 49 years and 75% subjects were aged 50 years and older. The majority of subjects were White (78%), followed by Asian (16%), Black (2%), and other racial groups (3%); 3% were of American Hispanic or Latino ethnicity; 37% were female.

Solicited Adverse Reactions: Solicited local adverse reactions reported within 7 days following administration of SHINGRIX (both doses combined) in auHSCT recipients (aged 18 through 49 and ≥50 years) were pain (88% and 83%), redness (30% and 35%), and swelling (21% and 18%). Solicited general adverse reactions reported within 7 days following administration of SHINGRIX (both doses combined) in auHSCT recipients (aged 18 through 49 and ≥50 years) were fatigue (64% and 54%), myalgia (58% and 52%), headache (44% and 30%), gastrointestinal symptoms (21% and 28%), shivering (31% and 25%), and fever (28% and 18%). The percentages of subjects aged 18 years and older reporting each solicited local and general adverse reaction following administration of each dose of SHINGRIX or placebo in the auHSCT study (NCT01610414) are presented in Table 3.

Table 3. Adult auHSCT Recipients (NCT01610414): Percentage of Subjects with Solicited Local and General Adverse Reactions within 7 Daysa of Vaccination in Adults Aged 18 Through 49 Years and 50 Years and Older by Dose (Total Vaccinated Cohort)
Adverse Reactions | Aged 18 Through 49 Years |  |  |  | Aged ≥50 Years
Adverse Reactions | SHINGRIX |  | Placebob |  | SHINGRIX |  | Placebob
 | Dose 1 | Dose 2 | Dose 1 | Dose 2 | Dose 1 | Dose 2 | Dose 1 | Dose 2
Local Adverse Reactions | n = 223 % | n = 205 % | n = 217 % | n = 207 % | n = 673 % | n = 635 % | n = 673 % | n = 627 %
Pain | 81 | 82 | 8 | 6 | 75 | 74 | 6 | 5
Pain, Grade 3c | 11 | 11 | 1 | 0 | 5 | 7 | 0.3 | 0
Redness | 20 | 25 | 0 | 0 | 21 | 28 | 1 | 1
Redness, >100 mm | 1 | 2 | 0 | 0 | 1 | 3 | 0 | 0
Swelling | 14 | 17 | 0 | 0 | 10 | 15 | 1 | 1
Swelling, >100 mm | 0 | 2 | 0 | 0 | 0.1 | 1 | 0 | 0
General Adverse Reactions | n = 222 % | n = 203; % | n = 218 % | n = 207 % | n = 674 % | n = 633 % | n = 674 % | n = 628 %
Myalgia | 41 | 51 | 22 | 21 | 37 | 43 | 18 | 17
Myalgia, Grade 3d | 4 | 8 | 2 | 2 | 2 | 4 | 1 | 1
Fatigue | 49 | 51 | 34 | 25 | 37 | 46 | 31 | 26
Fatigue, Grade 3d | 6 | 10 | 1 | 2 | 3 | 4 | 2 | 3
Headache | 23 | 38 | 17 | 17 | 15 | 25 | 13 | 8
Headache, Grade 3d | 1 | 5 | 0 | 2 | 0.1 | 2 | 0.4 | 1
Shivering | 20 | 26 | 12 | 6 | 11 | 21 | 7 | 7
Shivering, Grade 3d | 1 | 6 | 0 | 0 | 0.4 | 3 | 1 | 0.2
Fever, ≥37.5°C/99.5°F | 9 | 28 | 4 | 2 | 6 | 15 | 3 | 4
Fever, Grade 3 >39.5°C/103.1°F | 0 | 1 | 0 | 0 | 0.1 | 0.2 | 0 | 0.2
GIe | 14 | 13 | 13 | 12 | 18 | 18 | 16 | 12
GI, Grade 3d | 1 | 1 | 0 | 1 | 1 | 2 | 1 | 2
Total vaccinated cohort (TVC) for safety included all subjects with at least 1 documented dose (n).
% = Percentage of subjects reporting the symptom at least once.
a 7 days included day of vaccination and the subsequent 6 days.
b Placebo was sucrose reconstituted with saline solution.
c Grade 3 pain: defined as significant pain at rest preventing normal everyday activities.
d Grade 3 myalgia, fatigue, headache, shivering, and GI: defined as preventing normal activity.
e GI = Gastrointestinal symptoms including nausea, vomiting, diarrhea, and/or abdominal pain.

In general, the reported frequencies of solicited local and general adverse reactions in the other studies in immunocompromised populations were similar to that in the auHSCT study (NCT01610414). The local and general adverse reactions seen with SHINGRIX had a median duration of 1 to 3 days across all studies enrolling immunocompromised subjects.

Unsolicited Adverse Events: Across all 6 studies enrolling immunocompromised subjects, unsolicited adverse events, including both serious and non-serious events, occurring within 30 days following each vaccination were reported in 46% and 44% of subjects who received SHINGRIX or placebo. Adverse events of arthralgia, infective pneumonia, and influenza-like illness occurred in ≥1% of recipients of SHINGRIX and at a rate at least 1.5-fold higher than placebo (1.5% versus 1.0%, 1.5% versus 0.9%, and 1.3% versus 0.6%, respectively).

Serious Adverse Events: Across all 6 studies enrolling immunocompromised subjects, SAEs were reported at similar rates in subjects who received SHINGRIX (7%) or placebo (8%) from the first administered dose up to 30 days post-last vaccination. SAEs were reported for 26% of subjects who received SHINGRIX and for 27% of subjects who received placebo from the first administered dose up to 1 year post-last vaccination. SAEs of infective pneumonia were reported for 21 subjects (1.3%) who received SHINGRIX and for 11 subjects (0.7%) who received placebo up to 30 days post-last vaccination. Available information is insufficient to determine a causal relationship to vaccination.

Deaths: Across all 6 studies enrolling immunocompromised subjects, from the first administered dose up to 30 days post‑last vaccination, deaths were reported for 2 subjects (0.1%) who received SHINGRIX and 7 subjects (0.5%) who received placebo. From the first administered dose up to 1 year post-last vaccination, deaths were reported for 6% of subjects who received SHINGRIX and for 6% of subjects who received placebo. Causes of death among subjects were consistent with those expected in the populations evaluated.

Potential Immune-Mediated Diseases: Across all 6 studies enrolling immunocompromised subjects, new onset pIMDs or exacerbation of existing pIMDs were reported for 1.3% of subjects who received SHINGRIX and 1.0% of subjects who received placebo from the first administered dose up to 1 year post-last vaccination. There were no notable imbalances in specific pIMDs between treatment groups.

Other Medically Relevant Events: In the auHSCT study (NCT01610414), relapse or progression was reported by 315 of 922 subjects (34%) who received at least 1 dose of SHINGRIX and 331 of 924 subjects (36%) who received placebo from the first vaccination to study end.

In the auHSCT study (NCT00920218), relapse or progression was reported by 17 of 59 subjects (29%) who received at least 1 dose of SHINGRIX and 8 of 30 subjects (27%) who received placebo from the first vaccination to study end.

In the hematologic malignancy study, relapse or progression was reported by 45 of 283 subjects (16%) who received at least 1 dose of SHINGRIX and 58 of 279 subjects (21%) who received placebo from the first vaccination to study end.

In the renal transplant study, biopsy‑confirmed allograft rejection was reported by 4 of 132 (3%) of subjects who received SHINGRIX and by 7 of 132 (5%) of subjects who received placebo from the first vaccination to study end (approximately 13 months later). Creatinine as a measure of graft function and changes in alloimmunity postvaccination were not systematically evaluated.

In the HIV study, at least 1 event of worsening HIV condition was reported by 9 of 74 (12%) of subjects who received SHINGRIX and by 5 of 49 (10%) of subjects who received placebo from the first vaccination to study end.

Concomitant Administration with 23-Valent Pneumococcal Polysaccharide Vaccine

In an open‑label clinical study (NCT02045836) in subjects aged 50 years and older, information about solicited local and systemic adverse reactions was collected using diary cards for 7 days (i.e., day of vaccination and the next 6 days). When PNEUMOVAX 23 was concomitantly administered with the first dose of SHINGRIX compared to when the first dose of SHINGRIX was given alone, a greater percentage of subjects reported fever, defined as ≥37.5°C/99.5°F (16% vs. 7%, respectively) and shivering (21% vs. 7%, respectively) [see Clinical Studies (14.8)].

6.2 Postmarketing Experience

The following adverse reactions have been identified during postapproval use of SHINGRIX. Because these reactions are reported voluntarily from a population of uncertain size, it is not always possible to reliably estimate their frequency or establish a causal relationship to the vaccine.

General Disorders and Administration Site Conditions

Decreased mobility of the injected arm which may persist for 1 or more weeks, injection site induration.

Immune System Disorders

Hypersensitivity reactions, including angioedema, rash, and urticaria.

Nervous System Disorders

Guillain‑Barré syndrome.

Postmarketing Observational Studies of the Risk of Guillain‑Barré Syndrome following Vaccination with SHINGRIX

The association between vaccination with SHINGRIX and GBS was evaluated among Medicare beneficiaries aged 65 years or older in two studies. The results of each of these studies suggest a causal association of GBS with SHINGRIX.

In one study, using Medicare claims data, from October 2017 through February 2020, vaccinations with SHINGRIX among beneficiaries were identified through National Drug Codes, and potential cases of hospitalized GBS among recipients of SHINGRIX were identified through International Classification of Diseases codes.

The risk of GBS following vaccination with SHINGRIX was assessed in self‑controlled case series analyses using a risk window of 1 to 42 days postvaccination and a control window of 43 to 183 days postvaccination. Medical record review of GBS cases was conducted to estimate the Positive Predictive Value (PPV) of the claims algorithm. PPV‑adjusted risk estimates were calculated by imputing GBS status for all claims‑identified cases. These analyses included GBS cases in which other vaccinations were administered the same day or within 42 days of SHINGRIX. The primary analysis, which did not distinguish between doses, found an increased risk of GBS during the 42 days following vaccination with SHINGRIX, with an estimated 3 excess cases (95% confidence interval [CI]: 0.6, 5.6) of GBS per million doses administered to adults aged 65 years or older. In secondary analyses, an increased risk of GBS was observed during the 42 days following the first dose of SHINGRIX, with an estimated 6 excess cases (95% CI: 3.4, 9.6) of GBS per million doses administered to adults aged 65 years or older, and no increased risk of GBS was observed following the second dose of SHINGRIX.

A separate similarly-designed study also evaluated the association between vaccination with SHINGRIX and GBS among Medicare beneficiaries aged 65 years or older. Using Medicare claims data, from January 2018 through December 2020, vaccinations with SHINGRIX among beneficiaries were identified through National Drug Codes and Current Procedural Terminology codes. Potential cases of hospitalized GBS among recipients of SHINGRIX were identified through International Classification of Diseases codes.

The risk of GBS following vaccination with SHINGRIX was assessed in self-controlled risk interval analyses using a risk window of 1 to 42 days postvaccination and a control window of 43 to 84 days postvaccination. Medical record review was not conducted in this study and PPV adjustment was not performed. The primary and secondary analyses included GBS cases in which other vaccinations were administered the same day or within 42 days of SHINGRIX. The primary analysis, which did not distinguish between doses, found an increased risk of GBS during the 42 days following vaccination with SHINGRIX, with an estimated 7 excess cases (95% CI 4.4, 8.0) of GBS per million doses administered to adults aged 65 years or older. This analysis of GBS diagnoses in claims data was supported by a post hoc analysis excluding GBS cases in individuals who received pneumococcal, influenza, and/or tetanus, diphtheria and pertussis (Tdap) vaccines on the same day or in the 42 days prior to SHINGRIX vaccination. In secondary analyses, an increased risk of GBS was observed during the 42 days following the first dose of SHINGRIX, with an estimated 12 excess cases (95% CI 8.9, 13.4) of GBS per million doses administered to adults aged 65 years or older, and no increased risk of GBS was observed following the second dose of SHINGRIX.

8 USE IN SPECIFIC POPULATIONS

8.1 Pregnancy

Risk Summary

All pregnancies have a risk of birth defect, loss, or other adverse outcomes. In the U.S. general population, the estimated background risk of major birth defects and miscarriage in clinically recognized pregnancies is 2% to 4% and 15% to 20%, respectively. The data are insufficient to establish if there is vaccine-associated risk with SHINGRIX in pregnant women.

A developmental toxicity study was performed in female rats administered SHINGRIX or the AS01B adjuvant alone prior to mating, during gestation, and during lactation. The total dose was 0.2 mL on each occasion (a single human dose of SHINGRIX is 0.5 mL). This study revealed no adverse effects on fetal or pre-weaning development due to SHINGRIX (see Data).

Data

Animal Data: In a developmental toxicity study, female rats were administered SHINGRIX or the AS01B adjuvant alone by intramuscular injection 28 and 14 days prior to mating, on gestation Days 3, 8, 11, and 15, and on lactation Day 7. The total dose was 0.2 mL on each occasion (a single human dose of SHINGRIX is 0.5 mL). No adverse effects on pre‑weaning development up to postnatal Day 25 were observed. There were no vaccine-related fetal malformations or variations.

8.2 Lactation

Risk Summary

It is not known whether SHINGRIX is excreted in human milk. Data are not available to assess the effects of SHINGRIX on the breastfed infant or on milk production/excretion.

The developmental and health benefits of breastfeeding should be considered along with the mother’s clinical need for SHINGRIX and any potential adverse effects on the breastfed child from SHINGRIX or from the underlying maternal condition. For preventive vaccines, the underlying maternal condition is susceptibility to disease prevented by the vaccine.

8.4 Pediatric Use

Safety and effectiveness in individuals younger than 18 years have not been established. SHINGRIX is not indicated for prevention of primary varicella infection (chickenpox).

8.5 Geriatric Use

Adults Aged 60 Years and Older

Of the total number of subjects who received at least 1 dose of SHINGRIX in Studies 1 and 2 (n = 14,645), 2,243 (15%) were aged 60 through 69 years, 6,837 (47%) were aged 70 through 79 years, and 1,921 (13%) were aged 80 years and older. There were no clinically meaningful differences in efficacy across the age groups. [See Clinical Studies (14.1, 14.2, 14.3).]

The frequencies of solicited local and general adverse reactions in subjects aged 70 years and older were lower than in younger adults (aged 50 through 69 years). [See Adverse Reactions (6.1).]

Of the total number of subjects who received at least 1 dose of SHINGRIX in Studies 1 and 2 and were enrolled into the long‑term follow‑up (LTFU) study (n = 7,408), 1,262 (17%) were aged 60 through 69 years, 3,428 (46%) were aged 70 through 79 years, and 642 (9%) were aged 80 years and older at the time of initial vaccination. From a median of 5.6 years after vaccination to a median of 11.4 years after vaccination, incidence rates of HZ were higher in older age groups (aged 70 through 79 and ≥80 years) compared with younger age groups (aged 50 through 59 and 60 through 69 years). [See Clinical Studies (14.5).]

Immunocompromised Adults Aged 65 Years and Older

Of the total number of subjects who received at least 1 dose of SHINGRIX in the auHSCT study (n = 922), 172 (18.7%) were aged 65 years and older [see Clinical Studies (14.6)]. There were no clinically meaningful differences in efficacy between these subjects and younger adults (aged 18 through 64 years).

Of the total number of subjects who received at least 1 dose of SHINGRIX across the 6 studies in immunocompromised subjects (n = 1,587), 337 (21.2%) were aged 65 years and older. The frequencies of solicited local and general adverse reactions in subjects aged 65 years and older were generally similar to or lower than those reported by younger adults (aged 18 through 64 years).

11 DESCRIPTION

SHINGRIX (Zoster Vaccine Recombinant, Adjuvanted) is a sterile injectable suspension for intramuscular use that contains recombinant varicella zoster virus gE antigen adjuvanted with AS01B.

The vial and vial presentation is supplied as a vial of lyophilized recombinant varicella zoster virus surface gE antigen component (Lyophilized gE Antigen Component), which must be reconstituted at the time of use with the accompanying vial of AS01B (Adjuvant Suspension Component) to form SHINGRIX.

The SHINGRIX prefilled syringe presentation does not require reconstitution.

SHINGRIX is a sterile, opalescent, colorless to pale brownish liquid.

The gE antigen is obtained by culturing genetically engineered Chinese Hamster Ovary cells, which carry a truncated gE gene, in media containing amino acids, with no albumin, antibiotics, or animal‑derived proteins. The gE protein is purified by several chromatographic steps and formulated with excipients. The AS01B adjuvant is composed of 3‑O‑desacyl‑4’‑monophosphoryl lipid A (MPL) derived from Salmonella minnesota and QS‑21, a saponin purified from Quillaja saponaria Molina plant extract, and is combined in a liposomal formulation. The liposomes are composed of dioleoyl phosphatidylcholine (DOPC) and cholesterol in phosphate‑buffered saline solution containing disodium phosphate anhydrous, potassium dihydrogen phosphate, sodium chloride, and water for injection.

Each 0.5‑mL dose is formulated to contain 50 mcg of the recombinant gE antigen, 50 mcg of MPL, and 50 mcg of QS‑21. Each dose also contains 20 mg of sucrose, 4.385 mg of sodium chloride, 1 mg of DOPC, 0.54 mg of potassium dihydrogen phosphate, 0.25 mg of cholesterol, 0.160 mg of sodium dihydrogen phosphate dihydrate (applicable to prefilled syringe presentation only), 0.160 mg of sodium dihydrogen phosphate anhydrous (applicable to vial and vial presentation only), 0.15 mg of disodium phosphate anhydrous, 0.116 mg of dipotassium phosphate, and 0.08 mg of polysorbate 80. SHINGRIX does not contain preservatives. Each dose may also contain residual amounts of host cell proteins (≤3.0%) and DNA (≤2.1 picograms) from the manufacturing process.

In the vial and vial presentation, the vial stoppers are not made with natural rubber latex. In the prefilled syringe presentation, the tip cap and rubber plunger stopper are not made with natural rubber latex.

12 CLINICAL PHARMACOLOGY

12.1 Mechanism of Action

The risk of developing HZ, which increases with age and with immunosuppression due to disease and/or therapy, appears to be related to a decline in varicella zoster virus (VZV)-specific immunity. SHINGRIX was shown to boost VZV-specific immune response, which is thought to be the mechanism by which it protects against zoster disease [see Clinical Studies (14)].

13 NONCLINICAL TOXICOLOGY

13.1 Carcinogenesis, Mutagenesis, Impairment of Fertility

SHINGRIX has not been evaluated for its carcinogenic or mutagenic potential. Vaccination of female rats with SHINGRIX had no effect on fertility [see Use in Specific Populations (8.1)]. In a male fertility study, rats were vaccinated with 0.1 mL of SHINGRIX (a single human dose is 0.5 mL) on 42, 28, and 14 days prior to mating. There were no effects on male fertility.

14 CLINICAL STUDIES

14.1 Efficacy in Subjects Aged 50 Years and Older

Study 1 was a randomized, placebo‑controlled, observer‑blind clinical study conducted in 18 countries. Randomization was stratified (8:5:3:1) by age: 50 through 59 years, 60 through 69 years, 70 through 79 years, and ≥80 years. The study excluded, among others, subjects who were immunocompromised, had a history of previous HZ, were vaccinated against varicella or HZ, and patients whose survival was not expected to be at least 4 years or with conditions that might interfere with study evaluations. Subjects were followed for the development of HZ and postherpetic neuralgia (PHN) for a median of 3.1 years (range: 0 to 3.7 years). Suspected HZ cases were followed prospectively for the development of PHN, an HZ‑related complication defined as HZ‑associated pain (rated as 3 or greater on a 0- to 10‑point scale by the study subject) occurring or persisting at least 90 days following the onset of rash in confirmed cases of HZ.

The primary efficacy analysis population (referred to as the modified Total Vaccinated Cohort [mTVC]) included 14,759 subjects aged 50 years and older who received 2 doses (0 and 2 months) of either SHINGRIX (n = 7,344) or placebo (n = 7,415) and did not develop a confirmed case of HZ within 1 month after the second dose. In the mTVC population, 61% were female; 72% were White, 19% were Asian, 1.7% were Black, and 7% were of other racial/ethnic groups. The mean age of subjects was 62.3 years.

Confirmed HZ cases were determined by either Polymerase Chain Reaction (PCR) (89.4%) or by a Clinical Evaluation Committee (10.6%).

Efficacy against Herpes Zoster

Compared with placebo, SHINGRIX significantly reduced the risk of developing HZ by 97.2% (95% CI: 93.7, 99.0) in subjects aged 50 years and older (Table 4).

Table 4. Efficacy of SHINGRIX on Incidence of Herpes Zoster Compared with Placebo in Study 1a (mTVCb)
Age Group; (Years) | SHINGRIX |  |  | Placebo |  |  | % Efficacy; (95% CI)
Age Group; (Years) | N | n | Incidence Rate of HZ per 1,000 Person-Years | N | n | Incidence Rate of HZ per 1,000 Person-Years | % Efficacy; (95% CI)
Overall (≥50)c | 7,344 | 6 | 0.3 | 7,415 | 210 | 9.1 | 97.2; (93.7, 99.0)
50 Through 59 | 3,492 | 3 | 0.3 | 3,525 | 87 | 7.8 | 96.6; (89.6, 99.3)
60 Through 69 | 2,141 | 2 | 0.3 | 2,166 | 75 | 10.8 | 97.4; (90.1, 99.7)
≥70 | 1,711 | 1 | 0.2 | 1,724 | 48 | 9.4 | 97.9; (87.9, 100.0)
N = Number of subjects included in each group; n = Number of subjects having at least 1 confirmed HZ episode; HZ = Herpes zoster; CI = Confidence Interval.
a Study 1: NCT01165177.
b mTVC = Modified Total Vaccinated Cohort defined as subjects who received 2 doses (0 and 2 months) of either SHINGRIX or placebo and did not develop a confirmed case of HZ within 1 month after the second dose.
c Primary study endpoint was based on confirmed HZ cases in subjects aged 50 years and older.

In a descriptive analysis, vaccine efficacy against HZ in subjects aged 50 years and older was 93.1% (95% CI: 81.3, 98.2) in the fourth year postvaccination.

Occurrence of Postherpetic Neuralgia

Among all subjects aged 50 years or older in the mTVC, no cases of PHN were reported in the vaccine group compared with 18 cases reported in the placebo group.

14.2 Efficacy in Subjects Aged 70 Years and Older

Study 2 was a randomized, placebo‑controlled, observer‑blind clinical study conducted in 18 countries. Randomization was stratified (3:1) by age: 70 through 79 years and ≥80 years. With the exception of age, the study exclusion criteria were the same as for Study 1. Subjects were followed for the development of HZ and PHN for a median of 3.9 years (range: 0 to 4.5 years). Suspected HZ cases were followed prospectively for the development of PHN as for Study 1.

The primary efficacy analysis population (mTVC) included 13,163 subjects aged 70 years and older who received 2 doses (0 and 2 months) of either SHINGRIX (n = 6,541) or placebo (n = 6,622) and did not develop a confirmed case of HZ within 1 month after the second dose. In the mTVC population, 55% were female; 78% were White, 17% were Asian, 1% were Black, and 4% were of other racial/ethnic groups. The mean age of subjects was 75.5 years.

Confirmed HZ cases were determined by either PCR (92.3%) or by a Clinical Evaluation Committee (7.7%).

Efficacy against Herpes Zoster

Vaccine efficacy results against HZ in subjects aged 70 years and older are shown in Table 5.

Table 5. Efficacy of SHINGRIX on Incidence of Herpes Zoster Compared with Placebo in Study 2a (mTVCb)
Age Group; (Years) | SHINGRIX |  |  | Placebo |  |  | % Efficacy; (95% CI)
Age Group; (Years) | N | n | Incidence Rate of HZ per 1,000 Person‑Years | N | n | Incidence Rate of HZ per 1,000 Person-Years | % Efficacy; (95% CI)
Overall (≥70)c | 6,541 | 23 | 0.9 | 6,622 | 223 | 9.2 | 89.8; (84.3, 93.7)
70 Through 79 | 5,114 | 17 | 0.9 | 5,189 | 169 | 8.8 | 90.0; (83.5, 94.3)
≥80 | 1,427 | 6 | 1.2 | 1,433 | 54 | 11.0 | 89.1; (74.7, 96.2)
N = Number of subjects included in each group; n = Number of subjects having at least 1 confirmed HZ episode; HZ = Herpes zoster; CI = Confidence Interval.
a Study 2: NCT01165229.
b mTVC = Modified Total Vaccinated Cohort defined as subjects who received 2 doses (0 and 2 months) of either SHINGRIX or placebo and did not develop a confirmed case of HZ within 1 month after the second dose.
c Primary study endpoint was based on confirmed HZ cases in subjects aged 70 years and older.

In a descriptive analysis, vaccine efficacy against HZ in subjects aged 70 years and older was 85.1% (95% CI: 64.5, 94.8) in the fourth year after vaccination.

Efficacy against Postherpetic Neuralgia

Among all subjects aged 70 years or older in the mTVC, 4 cases of PHN were reported in the vaccine group compared with 28 cases reported in the placebo group. Vaccine efficacy against PHN was 85.5% (95% CI: [58.5; 96.3]). The benefit of SHINGRIX in the prevention of PHN can be attributed to the effect of the vaccine on the prevention of HZ.

Reduction of Use of Pain Medication

Among subjects with confirmed HZ, the use of HZ-associated pain medications was reported for 10 of 23 subjects (43.5%) who received SHINGRIX and for 160 of 223 subjects (71.7%) who received placebo.

14.3 Pooled Efficacy Analyses across Studies 1 and 2

The efficacy of SHINGRIX to prevent HZ and PHN in subjects aged 70 years and older was evaluated by combining the results from Studies 1 and 2 through a pre-specified pooled analysis in the mTVC. A total of 8,250 and 8,346 subjects who received SHINGRIX and placebo, respectively, were included in the pooled mTVC analysis.

Efficacy against Herpes Zoster

Compared with placebo, SHINGRIX significantly reduced the risk of developing HZ by 91.3% (95% CI: 86.9, 94.5) in subjects aged 70 years and older (Table 6).

Table 6. Efficacy of SHINGRIX on Incidence of Herpes Zoster Compared with Placebo in Studies 1 and 2 (Pooled Dataa) (mTVCb)
Age Group; (Years) | SHINGRIX |  |  | Placebo |  |  | % Efficacy; (95% CI)
Age Group; (Years) | N | n | Incidence Rate of HZ per 1,000 Person-Years | N | n | Incidence Rate of HZ per 1,000 Person-Years | % Efficacy; (95% CI)
Overall (≥70)c | 8,250 | 25 | 0.8 | 8,346 | 284 | 9.3 | 91.3; (86.9, 94.5)
70 Through 79 | 6,468 | 19 | 0.8 | 6,554 | 216 | 8.9 | 91.3; (86.0, 94.9)
≥80 | 1,782 | 6 | 1.0 | 1,792 | 68 | 11.1 | 91.4; (80.2, 96.9)
N = Number of subjects included in each group; n = Number of subjects having at least 1 confirmed HZ episode; HZ = Herpes zoster; CI = Confidence Interval.
a Pooled data from Study 1: NCT01165177 (subjects ≥50 years) and Study 2: NCT01165229 (subjects ≥70 years).
b mTVC = Modified Total Vaccinated Cohort defined as subjects who received 2 doses (0 and 2 months) of either SHINGRIX or placebo and did not develop a confirmed case of HZ within 1 month after the second dose.
c Primary endpoint of pooled analysis was based on confirmed HZ cases in subjects aged 70 years and older.

Efficacy against Postherpetic Neuralgia

Table 7 compares the overall rates of PHN in the vaccine and placebo groups across both studies.

Table 7. Efficacy of SHINGRIX on Overall Incidence of Postherpetic Neuralgia Compared with Placebo in Studies 1 and 2 (Pooled Dataa) (mTVCb)
Age Group; (Years) | SHINGRIX |  |  | Placebo |  |  | % Efficacy; (95% CI)
Age Group; (Years) | N | n | Incidence Rate of PHNc per 1,000 Person-Years | N | n | Incidence Rate of PHN per 1,000 Person-Years | % Efficacy; (95% CI)
Overall (≥70) | 8,250 | 4 | 0.1 | 8,346 | 36 | 1.2 | 88.8; (68.7, 97.1)
70 Through 79 | 6,468 | 2 | 0.1 | 6,554 | 29 | 1.2 | 93.0; (72.5, 99.2)
≥80 | 1,782 | 2 | 0.3 | 1,792 | 7 | 1.1 | 71.2; (-51.5, 97.1)
N = Number of subjects included in each group; n = Number of subjects having at least 1 PHN; CI = Confidence Interval.
a Pooled data from Study 1: NCT01165177 (subjects ≥50 years) and Study 2: NCT01165229 (subjects ≥70 years).
b mTVC = Modified Total Vaccinated Cohort defined as subjects who received 2 doses (0 and 2 months) of either SHINGRIX or placebo and did not develop a confirmed case of HZ within 1 month after the second dose.
c PHN = Postherpetic neuralgia defined as HZ-associated pain rated as 3 or greater (on a 0- to 10-point scale) occurring or persisting at least 90 days following the onset of rash using Zoster Brief Pain Inventory questionnaire.

The benefit of SHINGRIX in the prevention of PHN can be attributed to the effect of the vaccine on the prevention of HZ. The efficacy of SHINGRIX in the prevention of PHN in subjects with confirmed HZ could not be demonstrated.

14.4 Immunological Evaluation to Support Dosing Schedule

A measure of the immune response that confers protection against HZ is unknown. Anti-gE antibody levels were measured by anti-gE enzyme-linked immunosorbent assay (gE ELISA) and were used to support the dosing schedule.

In an open-label clinical study, 238 subjects aged 50 years and older received SHINGRIX on either a 0- and 2-month or 0- and 6-month schedule. Non-inferiority of the 0- and 6-month schedule compared with the 0- and 2-month schedule based on anti-gE ELISA GMCs 1 month after the second dose was demonstrated.

14.5 Long-Term Follow-Up Study

An open‑label, LTFU study (NCT02723773) was conducted in subjects aged 50 years and older who received SHINGRIX in Studies 1 and 2.

The primary analysis population (mTVC) included subjects who received 2 doses of SHINGRIX in Studies 1 and 2 and did not develop a confirmed case of HZ within 1 month after the second dose. The mTVC included 7,273 subjects who were followed for the occurrence of HZ and PHN starting at a median of 5.6 years postvaccination in Studies 1 and 2 and ending at a median of 11.4 years postvaccination. Of the 7,273 subjects in the mTVC, 2,046 were aged 50 through 59 years (28%), 1,243 (17%) were aged 60 through 69 years, 3,359 (46%) were aged 70 through 79 years, and 625 (9%) were aged 80 years or older at the time of initial vaccination. Demographic distribution of subjects (by sex, race, and ethnicity) was similar to Studies 1 and 2.

Of the subjects in the mTVC, 15 subjects who developed HZ in Studies 1 and 2 were excluded from the HZ analysis (n = 7,258 subjects). Among subjects 50 through 59 years, 60 through 69 years, 70 through 79 years, and 80 years or older at the time of vaccination, the incidence rates of HZ over the duration of the LTFU study were 1.0, 1.3, 2.3, and 2.5 per 1,000 person‑years, respectively. In the LTFU study, the incidence rates by age group were higher than the incidence rates of HZ reported by age group in the SHINGRIX groups in Study 1 and in the pooled analysis of Studies 1 and 2 (which were 0.3, 0.3, 0.8, and 1.0 per 1,000 person‑years, respectively [see Tables 4 and 6]). The incidence rates were lower than those reported by age group in the placebo groups in Study 1 and in the pooled analysis of Studies 1 and 2 (which were 7.8, 10.8, 8.9 and 11.1 per 1,000 person‑years, respectively [see Tables 4 and 6]). In Studies 1 and 2, the median follow‑up time after vaccination was 3.1 and 3.9 years, respectively.

Of the subjects in the mTVC, 2 subjects who developed PHN in Studies 1 and 2 were excluded from the PHN analysis (n = 7,271 subjects). Over the duration of the LTFU study, 4 cases of PHN were reported in the SHINGRIX group. One case was reported in a subject aged 67 years and 3 cases were reported in subjects 70 years or older at the time of vaccination. The incidence rate of PHN among subjects 70 years or older was 0.1 per 1,000 person‑years. This incidence rate is the same as the incidence rate of PHN reported in the SHINGRIX group and lower than the incidence rate reported in the placebo group in the pooled analysis of Studies 1 and 2 (which was 1.2 per 1,000 person‑years [see Table 7]). The benefit of SHINGRIX in the prevention of PHN can be attributed to the effect of the vaccine on the prevention of HZ.

14.6 Efficacy in Immunocompromised Adults Aged 18 Years and Older

The efficacy of SHINGRIX was evaluated in 1 Phase 3 randomized, placebo-controlled, observer-blind clinical study in immunocompromised adults aged ≥18 years who received an auHSCT 50 to 70 days prior to Dose 1 and who were expected to receive prophylactic antiviral therapy for ≤6 months post-transplant. The efficacy of SHINGRIX was calculated post hoc in another randomized, placebo-controlled, observer-blind study in subjects with hematologic malignancies who received Dose 1 of SHINGRIX or placebo during or within 6 months of completing immunosuppressive chemotherapy. Each of these studies was conducted in the following regions: North America, Latin America, Europe, Asia, Africa (auHSCT study only), and Australia/New Zealand.

Efficacy in Subjects Aged 18 Years and Older: auHSCT Recipients

In the auHSCT study, subjects were followed for the development of HZ and PHN for a median of 21 months (range: 0 to 49.4 months). Suspected HZ cases were followed prospectively for the development of PHN as in Studies 1 and 2.

The primary efficacy analysis population (mTVC) for the auHSCT study included 1,721 subjects who received 2 doses of either SHINGRIX or placebo and did not develop a confirmed case of HZ within 1 month after the second dose. Confirmed HZ cases were determined by either PCR (83.7%) or by a Clinical Evaluation Committee (16.3%).

Efficacy against Herpes Zoster: Compared with placebo, SHINGRIX significantly reduced the risk of developing HZ in auHSCT recipients aged 18 years and older (Table 8).

Table 8. Efficacy of SHINGRIX on Incidence of Herpes Zoster Compared with Placebo in Immunocompromised Adults Aged ≥18 Years (mTVCa)
Clinical Studies | Age Group (Years) | SHINGRIX |  |  | Placebo |  |  | % Efficacy; (95% CI)
Clinical Studies | Age Group (Years) | N | n | Incidence Rate of HZ per 1,000 Person‑Years | N | n | Incidence Rate of HZ per 1,000 Person‑Years | % Efficacy; (95% CI)
auHSCTb | Overall (≥18)c | 870 | 49 | 30.0 | 851 | 135 | 94.3 | 68.2; (55.5, 77.6)
auHSCTb | 18 Through 49 | 213 | 9 | 21.5 | 212 | 29 | 76.0 | 71.8; (38.7, 88.3)
auHSCTb | ≥50 | 657 | 40 | 33.0 | 639 | 106 | 100.9 | 67.3; (52.6, 77.9)
auHSCT = Autologous, hematopoietic, stem cell transplant.
N = Number of subjects included in each group; n = Number of subjects having at least 1 confirmed HZ episode; HZ = Herpes zoster; CI = Confidence Interval.
a mTVC = Modified Total Vaccinated Cohort, defined as subjects who received 2 doses (0 and 1 to 2 months) of either SHINGRIX or placebo and did not develop a confirmed case of HZ within 1 month after the second dose. Follow-up was censored at the time of treatment for relapse.
b NCT01610414.
c Primary study endpoint was based on confirmed HZ cases in subjects aged ≥18 years.

Efficacy in Subjects Aged 18 Years and Older with Hematologic Malignancies

In the study of hematologic malignancies, the mean age was 57 years. The majority of subjects were White (71%), followed by Asian (25%), Black (0.4%), and other racial groups (4%); 5% were of American Hispanic or Latino ethnicity; and 41% were female. Subjects were followed for the development of HZ for a median of 11.1 months (range: 0 to 15.6 months). PHN was not assessed as a study endpoint.

In the hematologic malignancy study, the population for the post hoc efficacy analysis included 515 subjects who received 2 doses of either SHINGRIX or placebo and did not develop a confirmed case of HZ within 1 month after the second dose. Confirmed HZ cases were determined by either PCR (81.3%) or by a Clinical Evaluation Committee (18.7%). The post hoc analysis showed SHINGRIX was 87.2% (95% CI [44.2; 98.6]) effective against development of HZ. The incidence rate of HZ per 1,000 person-years was 8.5 versus 66.2 in the SHINGRIX and placebo groups, respectively.

Additional Efficacy Endpoints Evaluated in the auHSCT Study

Efficacy against Postherpetic Neuralgia: In a descriptive analysis, including all subjects aged ≥18 years in the mTVC, 1 case of PHN was reported in the vaccine group compared with 9 cases reported in the placebo group. Vaccine efficacy against PHN was 89.3% (95% CI: [22.5; 99.8]). The benefit of SHINGRIX in the prevention of PHN can be attributed to the effect of the vaccine on the prevention of HZ.

Herpes Zoster-Associated Pain: Subjects with suspected HZ rated their “worst” HZ-associated pain on a 10-point scale. Among subjects with confirmed HZ, 37 out of 49 subjects (75.5%) receiving SHINGRIX and 120 out of 135 subjects (88.9%) receiving placebo rated their “worst” HZ-associated pain as 3 or greater. In this subset of subjects, the median duration of “worst” HZ associated pain was 14 and 24 days, among SHINGRIX and placebo recipients, respectively.

14.7 Revaccination after Vaccination with ZOSTAVAX (Zoster Vaccine Live)

In an open-label clinical study (NCT02581410), subjects aged 65 years and older, who had been previously vaccinated with ZOSTAVAX more than 5 years prior to study enrollment (n = 215) or who had never been vaccinated with ZOSTAVAX (n = 215), received 1 dose of SHINGRIX at Months 0 and 2. Subjects who had never been vaccinated with ZOSTAVAX were matched to those who had been previously vaccinated with ZOSTAVAX according to the predefined variables of age (65 through 69, 70 through 79, and ≥80 years), sex, race/ethnicity, and medical condition (immune‑mediated diseases, diabetes mellitus, depression, pulmonary conditions, or heart conditions). The mean age was 71 years; 51% were female. All subjects were White and were not Hispanic or Latino.

The anti-gE antibody (Ab) concentration measured by ELISA 1 month following 2 doses of SHINGRIX in subjects who had previously been vaccinated with ZOSTAVAX was non-inferior to that of subjects who had never been vaccinated with ZOSTAVAX. The upper limit (UL) of the 95% confidence interval (CI) was 1.17 (success criterion <1.5) for the anti-gE Ab adjusted geometric mean concentration (GMC) ratio between subjects who had never been vaccinated with ZOSTAVAX and subjects who had been previously vaccinated with ZOSTAVAX. There was no evidence for interference in the immune response to SHINGRIX in subjects previously vaccinated with ZOSTAVAX.

14.8 Concomitant Administration with Other Vaccines

Concomitant Administration with Influenza Vaccine

In an open-label clinical study (NCT01954251), subjects aged 50 years and older received 1 dose each of SHINGRIX and quadrivalent influenza vaccine (FLUARIX QUADRIVALENT) at Month 0 and 1 dose of SHINGRIX at Month 2 (n = 413), or 1 dose of FLUARIX QUADRIVALENT at Month 0 and 1 dose of SHINGRIX at Months 2 and 4 (n = 415). The mean age of the population was 63 years; 52% were female. The majority of subjects were White (92%), followed by Asian (6%), and Black (2%); 0.4% were of American Hispanic or Latino ethnicity. There was no evidence for interference in the immune response to any of the antigens contained in SHINGRIX or the coadministered vaccine.

Concomitant Administration with PNEUMOVAX 23 (Pneumococcal Vaccine Polyvalent)

In an open-label clinical study (NCT02045836), subjects aged 50 years and older received 1 dose each of SHINGRIX and PNEUMOVAX 23 at Month 0 and 1 dose of SHINGRIX at Month 2 (n = 432), or 1 dose of PNEUMOVAX 23 at Month 0 and 1 dose of SHINGRIX at Months 2 and 4 (n = 433). The mean age of the population was 63 years; 60% were female. The majority of subjects were White (94%), followed by Black (2%), Asian (2%), and other racial groups (2%); 1% were of American Hispanic or Latino ethnicity.

The immune response to SHINGRIX, based on anti-gE Ab, was measured by ELISA 1 month after administration of the second dose of SHINGRIX. Immune responses to 12 of the 23 pneumococcal serotypes contained in PNEUMOVAX 23 were measured by multiplex opsonophagocytosis assay (MOPA) at 1 month after administration of the single dose of PNEUMOVAX 23. There was no evidence for interference in the immune response to the antigen contained in SHINGRIX or to the 12 evaluated antigens contained in PNEUMOVAX 23 when the two vaccines were administered concomitantly.

Concomitant Administration with PREVNAR 13 (Pneumococcal 13-valent Conjugate Vaccine [Diphtheria CRM197 Protein])

In an open-label clinical study (NCT03439657), subjects aged 50 years and older received 1 dose each of SHINGRIX and PREVNAR 13 at Month 0 and 1 dose of SHINGRIX at Month 2 (n = 449), or 1 dose of PREVNAR 13 at Month 0 and 1 dose of SHINGRIX at Months 2 and 4 (n = 463). The mean age of the population was 63 years; 60% were female. The majority of subjects were White (98%), followed by Black (2%); 0.4% were of American Hispanic or Latino ethnicity.

The immune response to SHINGRIX, based on anti-gE Ab, was measured by ELISA 1 month after administration of the second dose of SHINGRIX. Immune responses to the pneumococcal serotypes contained in PREVNAR 13 were measured by MOPA at 1 month after administration of the single dose of PREVNAR 13. There was no evidence for interference in the immune response to the antigens contained in SHINGRIX or PREVNAR 13 when the two vaccines were administered concomitantly.

Concomitant Administration with BOOSTRIX (Tetanus Toxoid, Reduced Diphtheria Toxoid and Acellular Pertussis Vaccine, Adsorbed)

In an open-label clinical study (NCT02052596), subjects aged 50 years and older received 1 dose each of SHINGRIX and BOOSTRIX at Month 0 and 1 dose of SHINGRIX at Month 2 (n = 412; concomitant administration group), or 1 dose of BOOSTRIX at Month 0 and 1 dose of SHINGRIX at Months 2 and 4 (n = 418; sequential administration group). The mean age of the population was 63 years; 54% were female. The majority of subjects were White (87%), followed by Black (11%), and other racial groups; 2% were of American Hispanic or Latino ethnicity.

The immune response to SHINGRIX, based on anti-gE Ab, was measured by ELISA 1 month after administration of the second dose of SHINGRIX. The immune response to BOOSTRIX (anti-D, anti-T, and antibodies to pertussis antigens) was measured 1 month after administration of the single dose of BOOSTRIX. Concomitant administration showed no evidence for interference in the immune response to the antigen contained in SHINGRIX or the antigens contained in BOOSTRIX, with the exception of one of the pertussis antigens (pertactin), which did not meet the non-inferiority criterion: the UL of the 95% CI for the adjusted GMC ratio (sequential administration group/concomitant administration group) for anti-pertactin antibody was 1.58 (non-inferiority criterion <1.5). The clinical significance of the reduced immune response to pertactin is unknown.

16 HOW SUPPLIED/STORAGE AND HANDLING

16.1 SHINGRIX Vial and Vial Presentation

SHINGRIX vial and vial presentation is supplied as 2 components: A single‑dose vial of Lyophilized gE Antigen Component (powder) which must be reconstituted with a single‑dose vial of Adjuvant Suspension Component (liquid) (packaged without syringes or needles).

Table 9. Vial and Vial Presentation for SHINGRIX
Presentation | Carton NDC Number | Components
Presentation | Carton NDC Number | Adjuvant Suspension Component (liquid) | Lyophilized gE Antigen Component (powder)
An outer carton of 10 doses | 58160-823-11 | 10 vials; NDC 58160-829-03 | 10 vials; NDC 58160-828-03

Storage before Reconstitution

Lyophilized gE Antigen Component and Adjuvant Suspension Component vials:

- Store refrigerated between 2°C and 8°C (36°F and 46°F).
- Protect vials from light. Do not freeze. Discard if frozen.

Storage after Reconstitution

- Administer immediately or store refrigerated between 2°C and 8°C (36°F and 46°F) for up to 6 hours prior to use.
- Discard reconstituted vaccine if not used within 6 hours.
- Do not freeze. Discard if frozen.

16.2 SHINGRIX Prefilled Syringe Presentation

SHINGRIX is available as 0.5‑mL single‑dose, disposable, prefilled TIP‑LOK syringes (Luer Lock syringes) packaged without needles. TIP‑LOK syringes are to be used with Luer Lock compatible needles.

Table 10. Prefilled Syringe Presentation for SHINGRIX
Presentation | Carton NDC Number | SHINGRIX NDC Number
An outer carton of 10 doses | 58160‑849‑52 | 0.5‑mL single‑dose, prefilled syringe; NDC 58160‑849‑43

- Store refrigerated between 2°C and 8°C (36°F and 46°F).
- Protect from light.
- Do not freeze. Discard if frozen.

Administer SHINGRIX as soon as possible after the prefilled syringe is removed from the refrigerator. SHINGRIX prefilled syringe may be kept for up to 72 hours at temperatures between 8°C and 25°C (46°F and 77°F).

17 PATIENT COUNSELING INFORMATION

- Inform patients of the potential benefits and risks of immunization with SHINGRIX and of the importance of completing the 2-dose immunization series according to the schedule.
- Inform patients about the potential for adverse reactions that have been temporally associated with administration of SHINGRIX.
- Provide the Vaccine Information Statements, which are available free of charge at the Centers for Disease Control and Prevention (CDC) website (www.cdc.gov/vaccines).

SHINGRIX, BOOSTRIX, FLUARIX QUADRIVALENT, and TIP‑LOK are trademarks owned by or licensed to the GSK group of companies. The other brands listed are trademarks owned by or licensed to their owners and are not owned by or licensed to the GSK group of companies. The makers of these brands are not affiliated with and do not endorse the GSK group of companies or its products.

Manufactured by GlaxoSmithKline Biologicals

Rixensart, Belgium, U.S. License 1617, and

Distributed by GlaxoSmithKline

Durham, NC 27701

©2026 GSK group of companies or its licensor.

SHX:11PI

PACKAGE LABEL

PRINCIPAL DISPLAY PANEL

NDC 58160-823-11

SHINGRIX

Zoster Vaccine Recombinant, Adjuvanted

Rx only

NOTICE: One vial of lyophilized powder and one vial of liquid suspension MUST BE COMBINED BEFORE USE

For 50 Years of Age and Older and For 18 Years of Age and Older who are Immunocompromised and at Increased Risk of Herpes Zoster

Contents (10 doses of SHINGRIX):

10 Vials containing Lyophilized gE Antigen Component

10 Vials containing Adjuvant Suspension Component

After reconstitution, a single dose of SHINGRIX is 0.5 mL

GSK

SHINGRIX

Antigen Made in Belgium, France, and Italy

Adjuvant Made in Belgium and Italy

©2024 GSK group of companies or its licensor.

Rev. 5/24
519797

10 Count Adjuvant Vial Label

NDC 58160-829-03

490658 Rev. 10/17

10 Count Antigen Vial Label

NDC 58160-828-03

490735 Rev. 10/17

PACKAGE LABEL

PRINCIPAL DISPLAY PANEL

NDC 58160-849-52

SHINGRIX

Zoster Vaccine Recombinant, Adjuvanted

Zoster

Rx only

GSK

DOES NOT REQUIRE RECONSTITUTION

Suspension for intramuscular injection

For 50 Years of Age and Older and For 18 Years of Age and Older who are Immunocompromised and at Increased Risk of Herpes Zoster

10 Disposable Single-Dose Prefilled TIP-LOK Syringes each containing one 0.5-mL dose

TIP-LOK syringes to be used with Luer Lock compatible needles

NEEDLES NOT INCLUDED

Prefilled Syringe

SHINGRIX

Made in Belgium

©2025 GSK group of companies or its licensor.

Rev. 4/25

523622